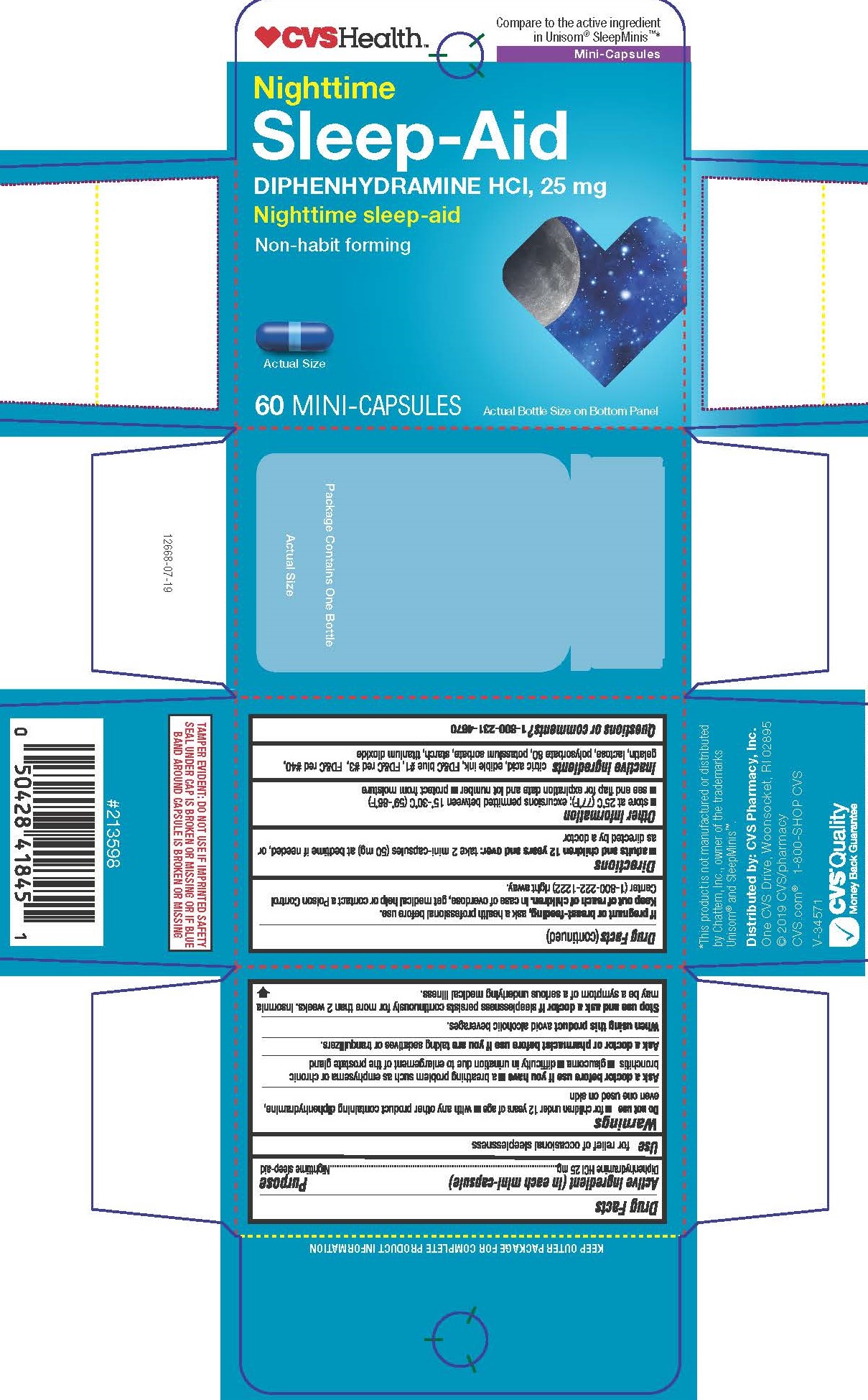 DRUG LABEL: Diphenhydramine HCl
NDC: 69842-537 | Form: CAPSULE
Manufacturer: CVS Pharmacy, Inc.
Category: otc | Type: HUMAN OTC DRUG LABEL
Date: 20241202

ACTIVE INGREDIENTS: DIPHENHYDRAMINE HYDROCHLORIDE 25 mg/1 1
INACTIVE INGREDIENTS: ANHYDROUS CITRIC ACID; FD&C BLUE NO. 1; LACTOSE MONOHYDRATE; FD&C RED NO. 40; POTASSIUM SORBATE; FD&C RED NO. 3; POLYSORBATE 80; GELATIN; STARCH, CORN; TITANIUM DIOXIDE

5347-CVS

Drug Facts

Active Ingredient (in each mini-capsule)

Diphenhydramine HCl 25mg

Purpose

Nighttime sleep-aid

Uses

for relief of occasional sleeplessness

WARNINGS

Do not use

- for children under 12 years of age
- with any other product containing diphenhydramine, even one used on skin

Ask a doctor before use if you have

- a breathing problem such as emphysema or chronic brochitis
- glaucoma
- difficulty in urination due to enlargement of the prostate gland

Ask a doctor or pharmacist before use if you are

taking sedatives or tranquilizers.

When using this product

avoid alcoholic beverages

Stop use and ask a doctor if

sleeplessness persists continuously for more than 2 weeks. Insomnia may be a symptom of a serious underlying medical illness

If pregnant or breast-feeding,

ask a health professional before use.

OVERDOSAGE

In case of overdose, get medical help or contact Poison Control Center (1-800-222-1222) right away.

Directions

- Adults and children 12 years and over: take 2 mini-capsules (50mg) at bedtime if nedded, or as directed by a doctor

Other Information

- Store at 25ºC(77ºF); excursions permitted between 15º-30ºC (59º-86ºF)
- see end flap for expiration date and lot number
- protect from moisture

INACTIVE INGREDIENT

citric acid, edible ink, FD&C blue #1, FD&C red #3, FD&C red #40, gelatin, lactose, polysorbate 80, potassium sorbate, starch, titanium dioxide

Question or comments?

1-800-231-4670

KEEP OUTER PACKAGE FOR COMPLETE PRODUCT INFORMATION

TAMPER EVIDENT: DO NOT USE IF IMPRINTED SAFETY SEAL UNDER CAP IS BROKEN OR MISSING OR IF BLUE

BAND AROUND CAPSULE IS BROKEN OR MISSING

*This product is not manufactured or distributed by Chattem, Inc., owner of the trademarks Unisom® and SleepMinis™.

Distributed by: CVS Pharmacy, Inc.

One CVS Drive, Woonsocket, RI 02895

PACKAGE LABEL

CVSHealth

Compare to the active ingredient in Unisom® SleepMinis™*

Nighttime Sleep-Aid

Diphenhydramine HCl, 25mg

Nighttime sleep-aid

Non-habit forming

60 Mini-Capsules